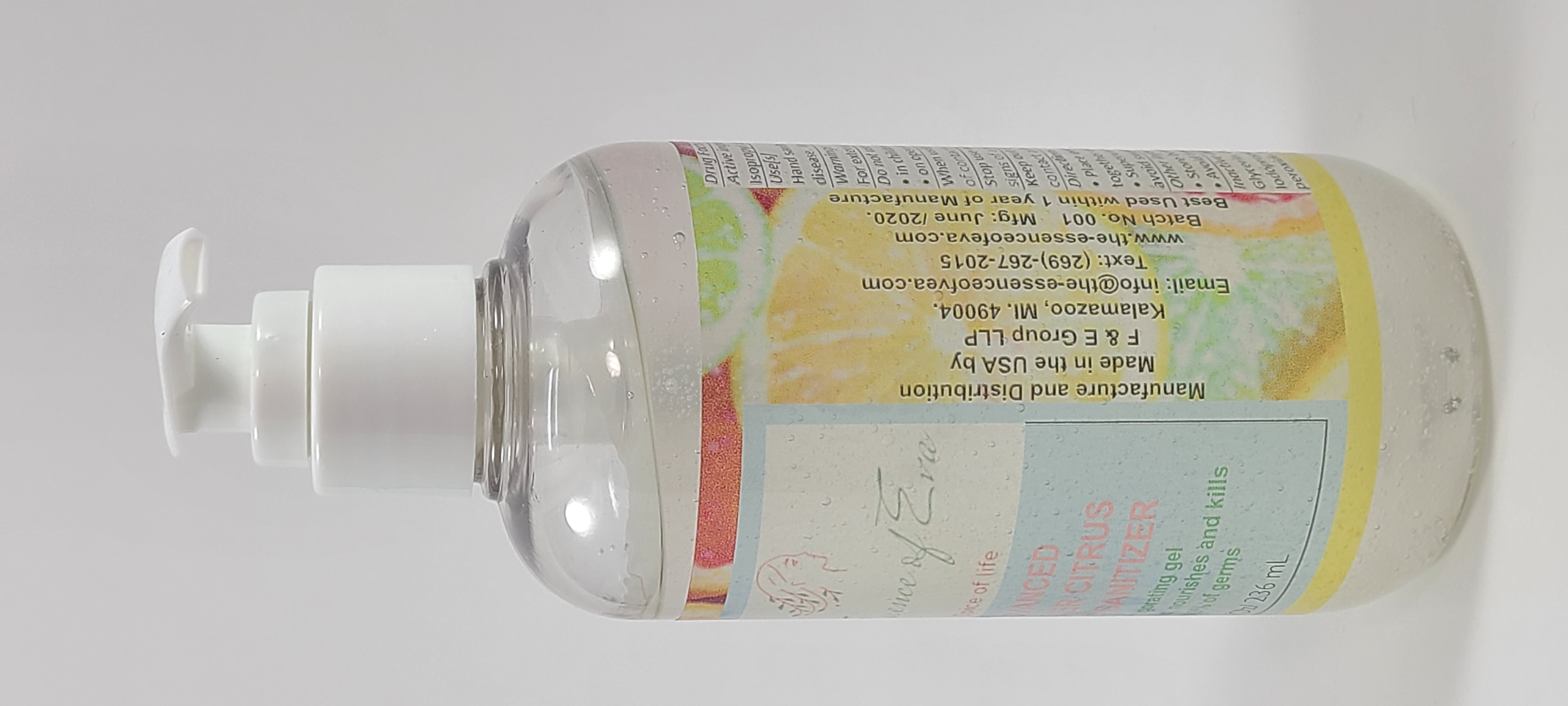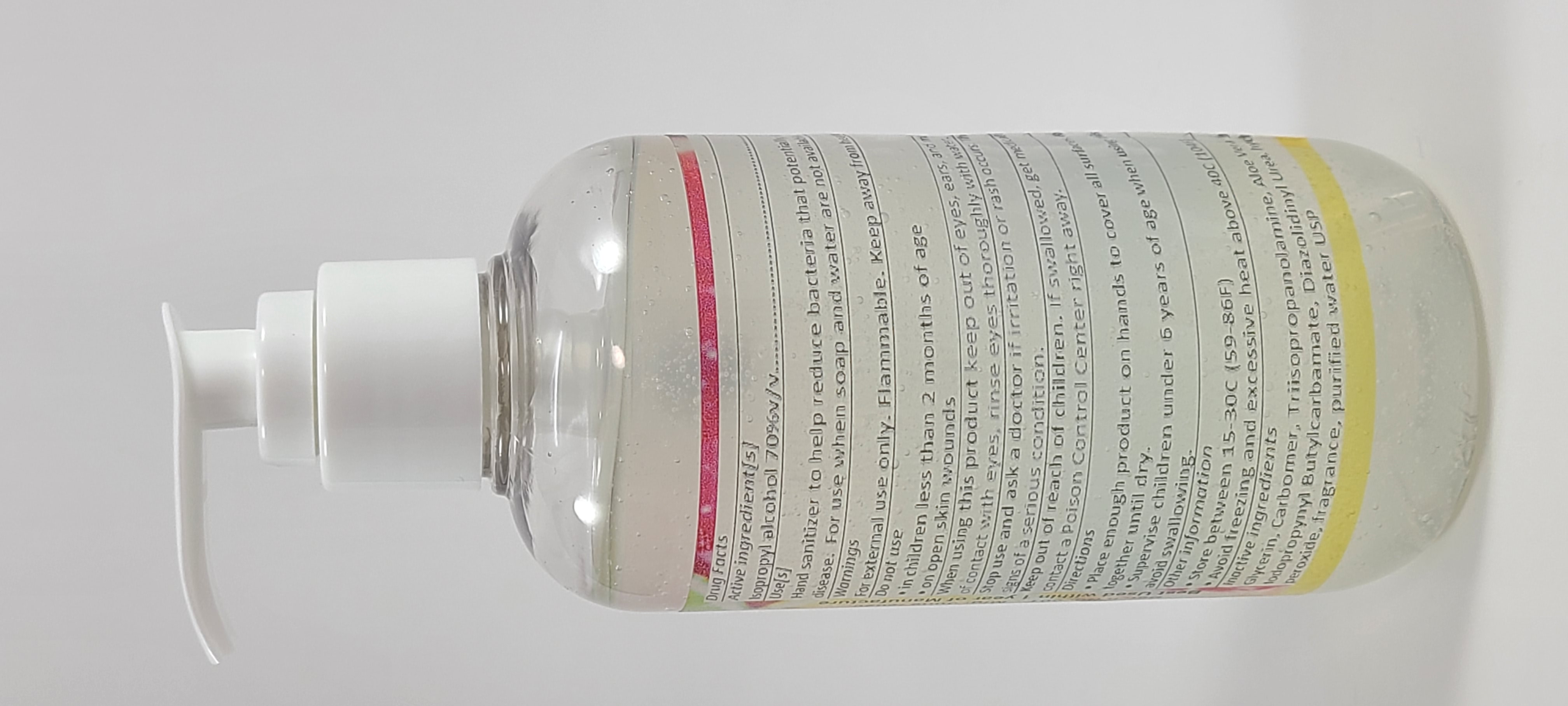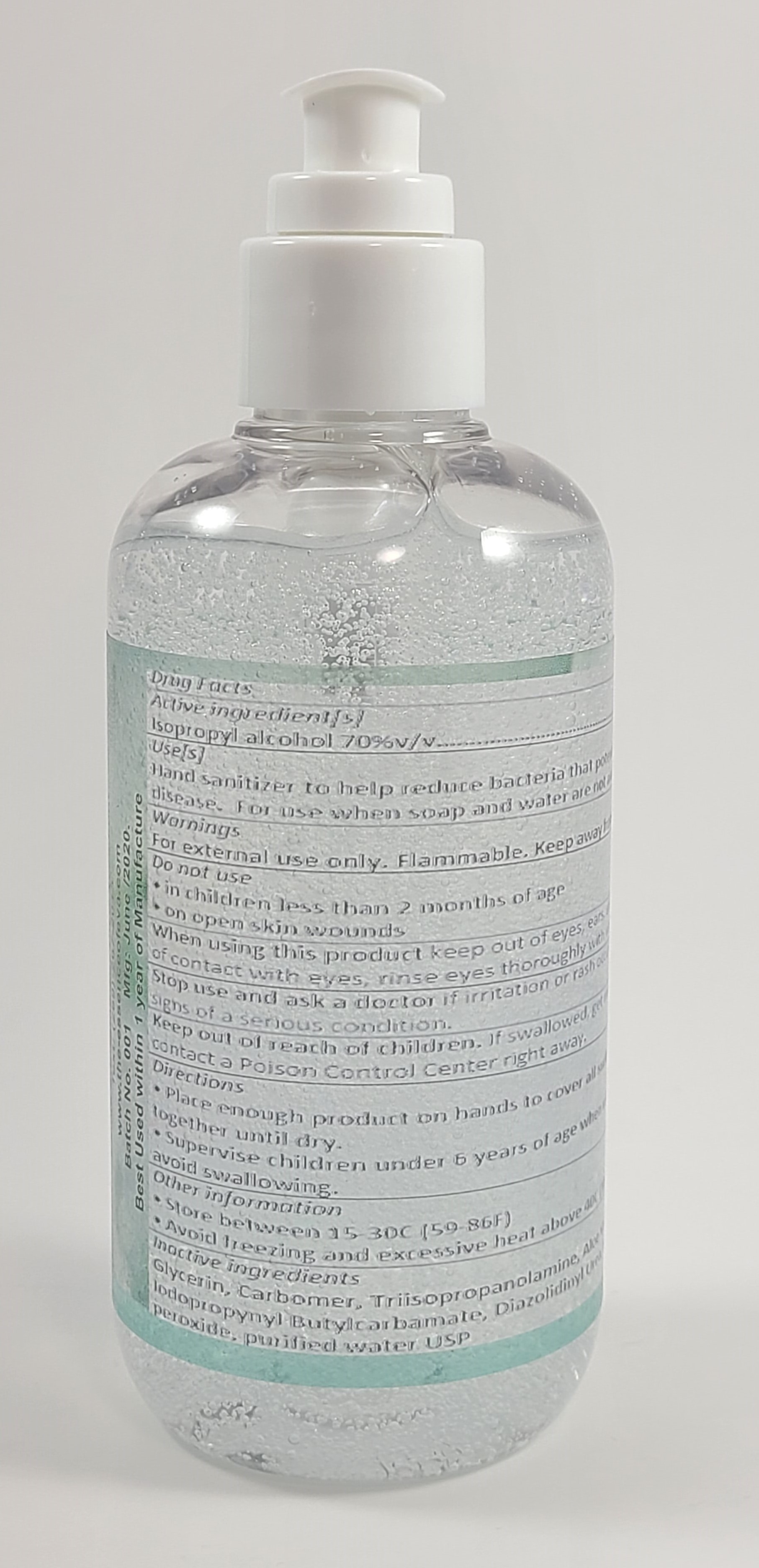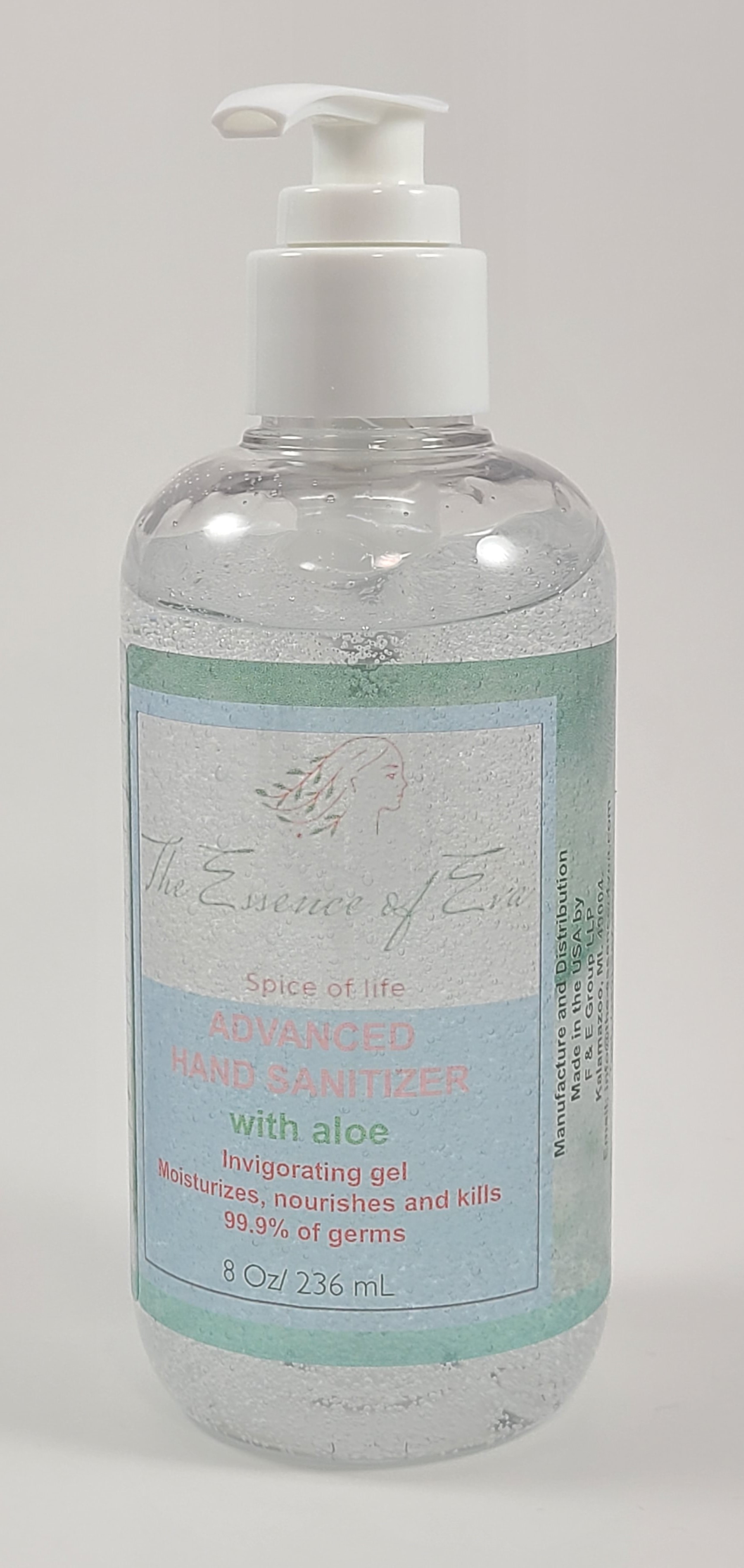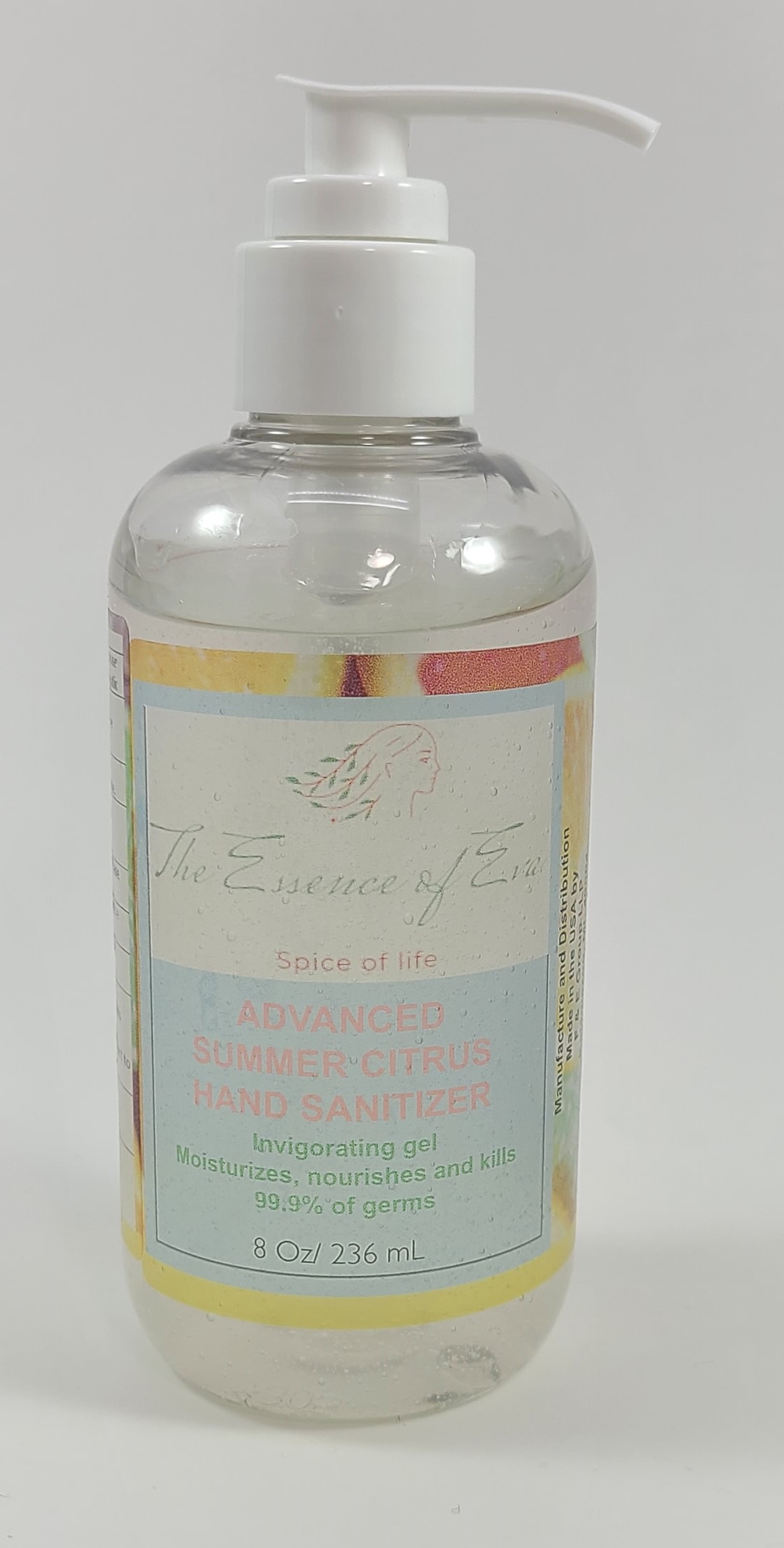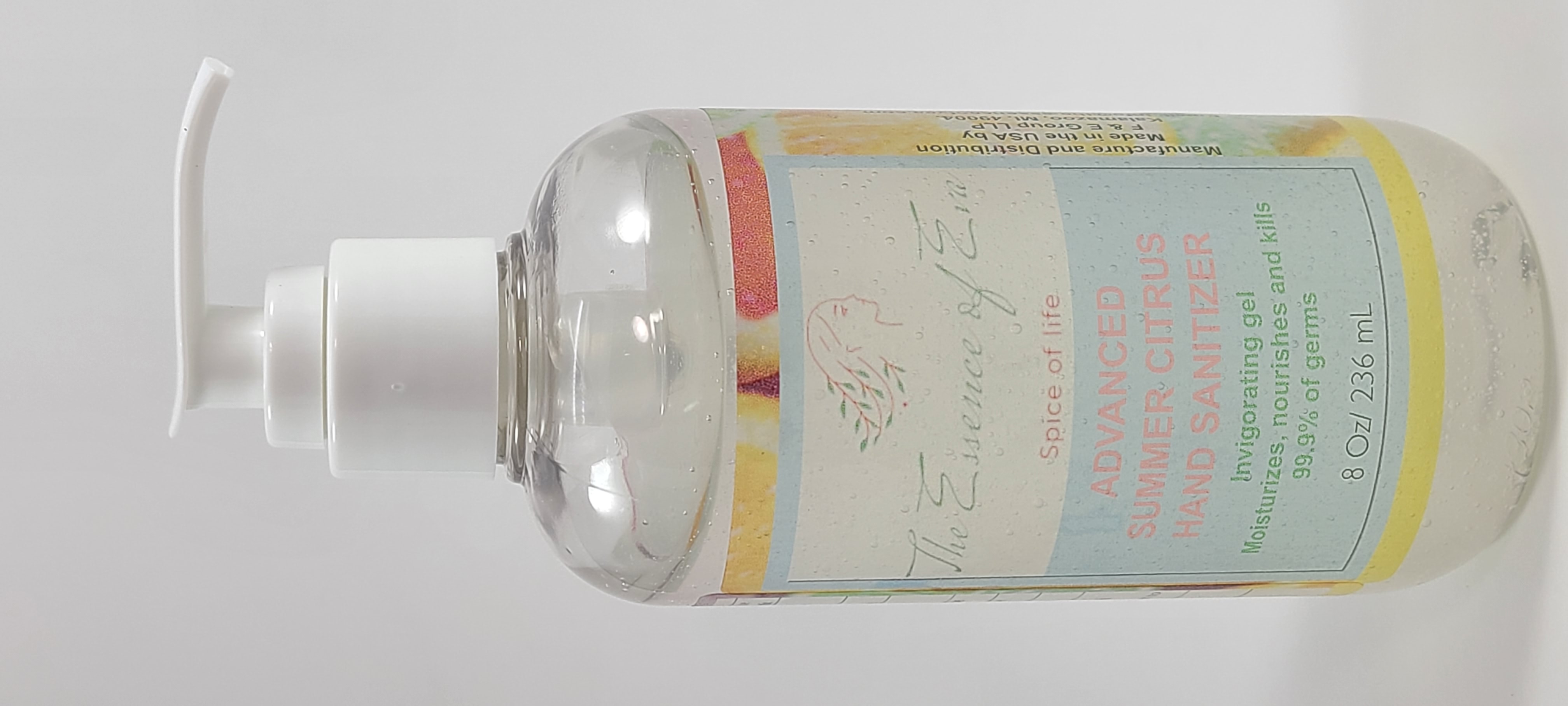 DRUG LABEL: The Essence of Eva
NDC: 79206-002 | Form: GEL
Manufacturer: F & E Group LLP
Category: otc | Type: HUMAN OTC DRUG LABEL
Date: 20211230

ACTIVE INGREDIENTS: ISOPROPYL ALCOHOL 70 mL/100 mL
INACTIVE INGREDIENTS: GLYCERIN 2 mL/100 mL; WATER 15 mL/100 mL; ALOE 35 mL/100 mL; HYDROGEN PEROXIDE 0.125 mL/100 mL

Active ingredient[s] Purpose

Isopropyl alcohol 70%v/v…….………….……………..................Antiseptic

PURPOSE

Use[s]

Hand sanitizer to help reduce bacteria that potentially can cause disease. For use when soap and water are not available.

Warnings

For external use only. Flammable. Keep away from heat or flame.

Do not use

• in children less than 2 months of age

• on open skin wounds

When using this product keep out of eyes, ears, and mouth. In case of contact with eyes, rinse eyes thoroughly with water.

Stop use and ask a doctor if irritation or rash occurs. These may be signs of a serious condition.

Keep out of reach of children. If swallowed, get medical help, or contact a Poison Control Center right away.

Directions

• Place enough product on hands to cover all surfaces. Rub hands together until dry.

• Supervise children under 6 years of age when using this product to avoid swallowing.

Other information

• Store between 15-30C (59-86F)

• Avoid freezing and excessive heat above 40C (104F)

NDC 79206-001

Inactive ingredients

Glycerin, Carbomer, Triisopropanolamine, Aloe Vera Juice, Iodopropynyl Butylcarbamate, Diazolidinyl Urea, hydrogen peroxide, fragrance, purified water USP

NDC 79206-002

Inactive ingredients

Glycerin, Carbomer, Triisopropanolamine, Aloe Vera Juice, Iodopropynyl Butylcarbamate, Diazolidinyl Urea, hydrogen peroxide, purified water USP

Directions

• Place enough product on hands to cover all surfaces. Rub hands together until dry.

• Supervise children under 6 years of age when using this product to avoid swallowing.